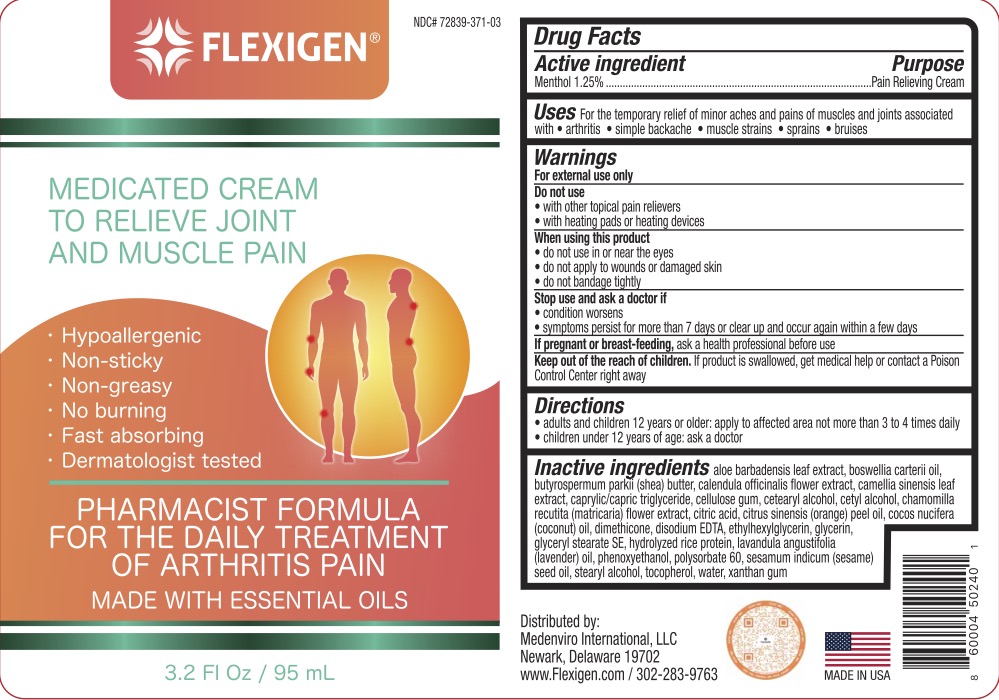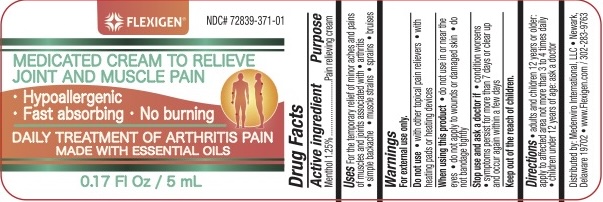 DRUG LABEL: Flexigen
NDC: 72839-371 | Form: CREAM
Manufacturer: Derma Care Research Labs, LLC
Category: otc | Type: HUMAN OTC DRUG LABEL
Date: 20240115

ACTIVE INGREDIENTS: MENTHOL 1.25 g/100 mL
INACTIVE INGREDIENTS: FRANKINCENSE OIL; SHEA BUTTER; GLYCERYL STEARATE SE; ALOE VERA LEAF; LAVENDER OIL; CARBOXYMETHYLCELLULOSE SODIUM; RICE BRAN; ETHYLHEXYLGLYCERIN; CETOSTEARYL ALCOHOL; CETYL ALCOHOL; WATER; XANTHAN GUM; GLYCERIN; CALENDULA OFFICINALIS FLOWER; CHAMOMILE; TOCOPHEROL; GREEN TEA LEAF; PHENOXYETHANOL; POLYSORBATE 60; MEDIUM-CHAIN TRIGLYCERIDES; SESAME OIL; STEARYL ALCOHOL; CITRIC ACID MONOHYDRATE; ORANGE PEEL; COCONUT OIL; DIMETHICONE 200; EDETATE DISODIUM

Flexigen, Menthol 1.25%

ACTIVE INGREDIENT

Menthol 1.25%

PURPOSE

Pain Relieving Cream

INDICATIONS AND USAGE

For the temporary relief of minor aches and pain associated with arthritis, simple backache, muscle strains, sprains, and bruises.

WARNINGS

For external use only. Do not use with other topical pain relievers, with heating pads or heating devices. When using this product do not use in or near the eyes, do not apply to wounds or damaged skin, do not bandage tightly. Stop use and ask a doctor if condition worsens, if symptoms persist for more than 7 days or clear up and occur again within a few days.

KEEP OUT OF REACH OF CHILDREN

If swallowed, get medical help or contact a Poison Control Center right away.

DOSAGE AND ADMINISTRATION

Adults and children 12 years of age and older, apply to the affected area not more than 3 to 4 times daily. Children under 12 years of age: ask a doctor.

INACTIVE INGREDIENT

Aloe Barbadensis Leaf Extract, Boswellia Carterii Oil, Butyrospermum Parkii (Shea) Butter, Calendula Officinalis Flower Extract, Camellia Sinensis Leaf Extract, Caprylic/Capric Triglyceride, Cellulose Gum, Cetearyl Alcohol, Cetyl Alcohol, Chamomilla Recutita (Matricaria) Flower Extract, Citric Acid, Citrus Sinensis (Orange) Peel Oil, Cocos Nucifera (Coconut) Oil, Dimethicone, Disodium EDTA, Ethylhexylglyerin, Glycerin, Glyceryl Stearate SE, Hydrolyzed Rice Protein, Lavandula Angustifolia (Lavender) Oil, Phenoxyethanol, Polysorbate 60, Sesamum Indicum (Sesame) Seed Oil, Stearyl Alcohol, Tocopherol, Water, Xanthan Gum.

PREGNANCY

If pregnant or breast-feeding, ask a health professional before use.